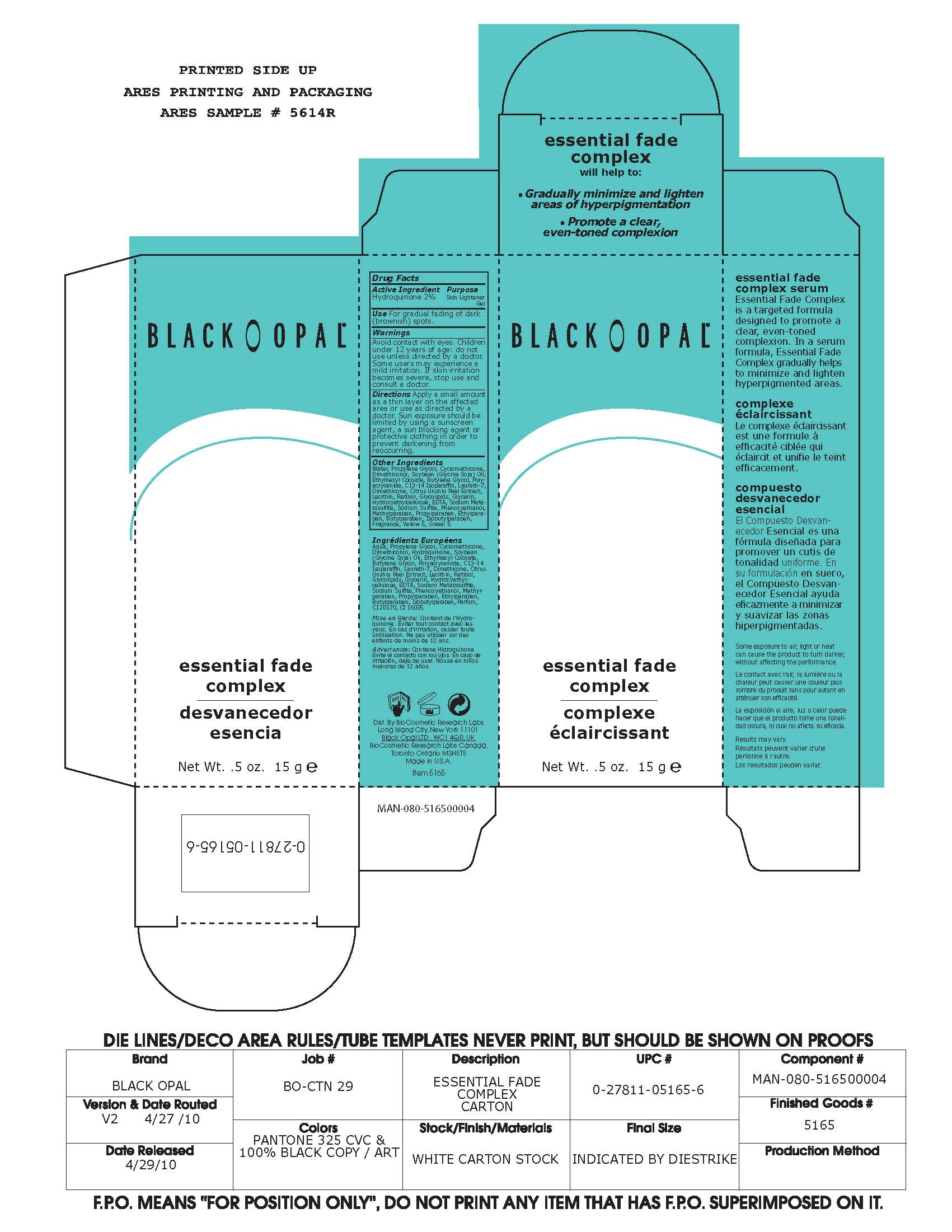 DRUG LABEL: Essential Fade Complex
NDC: 59735-318 | Form: GEL
Manufacturer: Biocosmetics Research Lab
Category: otc | Type: HUMAN OTC DRUG LABEL
Date: 20110120

ACTIVE INGREDIENTS: Hydroquinone 2 g/100 g
INACTIVE INGREDIENTS: Water

Essential Fade Complex

Active Ingredient

Hydroquinone 2%

Purpose

Skin Lightener Gel

INDICATIONS AND USAGE

Use For gradual fading of dark (brownish) spots.

Warnings

Avoid contact with eyes. Children under 12 years of age: do not use unless directed by a doctor. Some users may experience a mild irritation. If skin irritation becomes severe, stop use and consult a doctor.

DOSAGE AND ADMINISTRATION

Directions Apply a small amount as a thin layer on the affected area or use as directed by a doctor. Sun exposure should be limited by using a sunscreen agent, a sun blocking agent or protective clothing in order to prevent darkening from reoccurring.

INACTIVE INGREDIENT

Other Ingredients

Water, Propylene Glycol, Cyclomethicone, Dimethiconol, Soybean (Glycine Soja) Oil, Ethylhexyl Cocoate, Butylene Glycol, Polyacrylamide, C13-14 Isoparaffin, Laureth-7, Dimethicone, Citrus Unshiu Peel Extract, Lecithin, Retinol, Glycolipids, Glycerin, Hydroxyethylcellulose, EDTA, Sodium Metabisulfite, Sodium Sulfite, Phenoxyethanol, Methylparaben, Propylparaben, Ethylparaben, Butylparaben, Isobutylparaben, Fragrance, Yellow 5, Green 5.

Keep out of reach of children